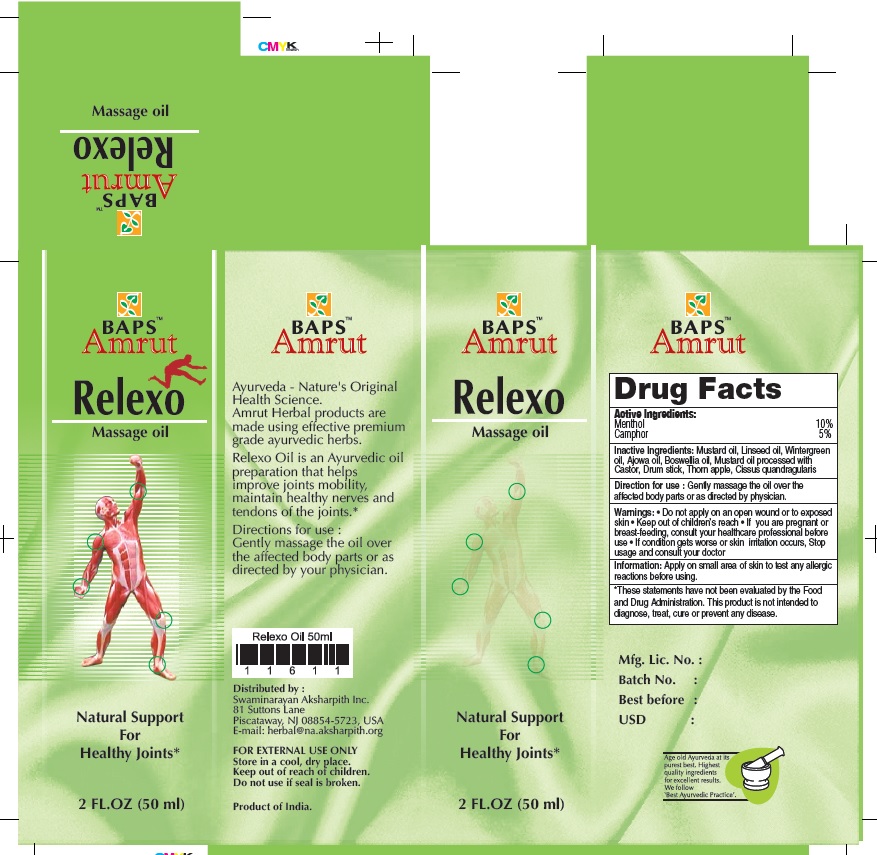 DRUG LABEL: Relexo Oil
NDC: 57631-116 | Form: OIL
Manufacturer: InvaTech Pharma Solutions LLC
Category: otc | Type: HUMAN OTC DRUG LABEL
Date: 20170419

ACTIVE INGREDIENTS: MENTHOL 5 1/1 mL; CAMPHOR (NATURAL) 2.5 1/1 mL
INACTIVE INGREDIENTS: MUSTARD OIL; LINSEED OIL; BOSWELLIA SERRATA RESIN OIL; CISSUS QUADRANGULARIS WHOLE

RELEXO MASSAGE OIL

Relexo Massage oil Active Ingredients

Menthol 10%

Camphor 5%

Purpose

Natural support for healthy joints

Uses

Temporary relieves minor aches and pains of muscles and joints associated with simple backache, arthritis, strains, bruises and sprains.

Inactive Ingredients

Mustard oil, Linseed oil, Wintergreen oil, Ajowa oil, Boswelia oil, Mustard oil processed with Castor, Drum stick, Thorn apple, Cissus quandragularis

Direction for use

Gently massage the oil over the affected body parts or as directed by physician.

Warnings

- Do not apply on an open wound or to exposed skin
- If you are pregnant or breast-feeding, consult your healthcare professional before use
- If condition gets worse or skin irritation occurs, stop usage and consult your doctor

Other Information

Apply on samll area of skin to test any allergic reactions before using.

(*These statements have not been evaluated by the Food and Drug Administration. This product is not intended to diagnose, treat, cure or prevent any disease.)